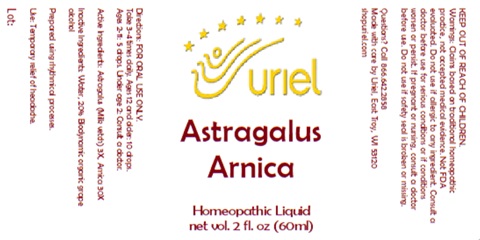 DRUG LABEL: Astragalus Arnica
NDC: 48951-1171 | Form: LIQUID
Manufacturer: Uriel Pharmacy Inc.
Category: homeopathic | Type: HUMAN OTC DRUG LABEL
Date: 20260227

ACTIVE INGREDIENTS: ASTRAGALUS PROPINQUUS ROOT 3 [hp_X]/1 mL; ARNICA MONTANA 30 [hp_X]/1 mL
INACTIVE INGREDIENTS: WATER; ALCOHOL

Astragalus Arnica

INDICATIONS AND USAGE

Directions: FOR ORAL USE ONLY.

DOSAGE AND ADMINISTRATION

Take 3-4 times daily. Ages 12 and older: 10 drops.
Ages 2-11: 5 drops. Under age 2: Consult a doctor.

Active Ingredients: Astragalus (Milk vetch) 3X, Arnica 30X

Inactive Ingredients: Water, 20% Biodynamic organic grape alcohol

Prepared using rhythmical processes.

PURPOSE

Use: Temporary relief of headache.

KEEP OUT OF REACH OF CHILDREN.

WARNINGS

Warnings: Claims based on traditional homeopathic practice, not accepted medical evidence. Not FDA evaluated. Do not use if allergic to any ingredient. Consult a doctor before use for serious conditions or if conditions worsen or persist. If pregnant or nursing, consult a doctor before use. Do not use if safety seal is broken or missing.

Questions? Call 866.642.2858
Made with care by Uriel, East Troy, WI 53120
shopuriel.com

Lot: